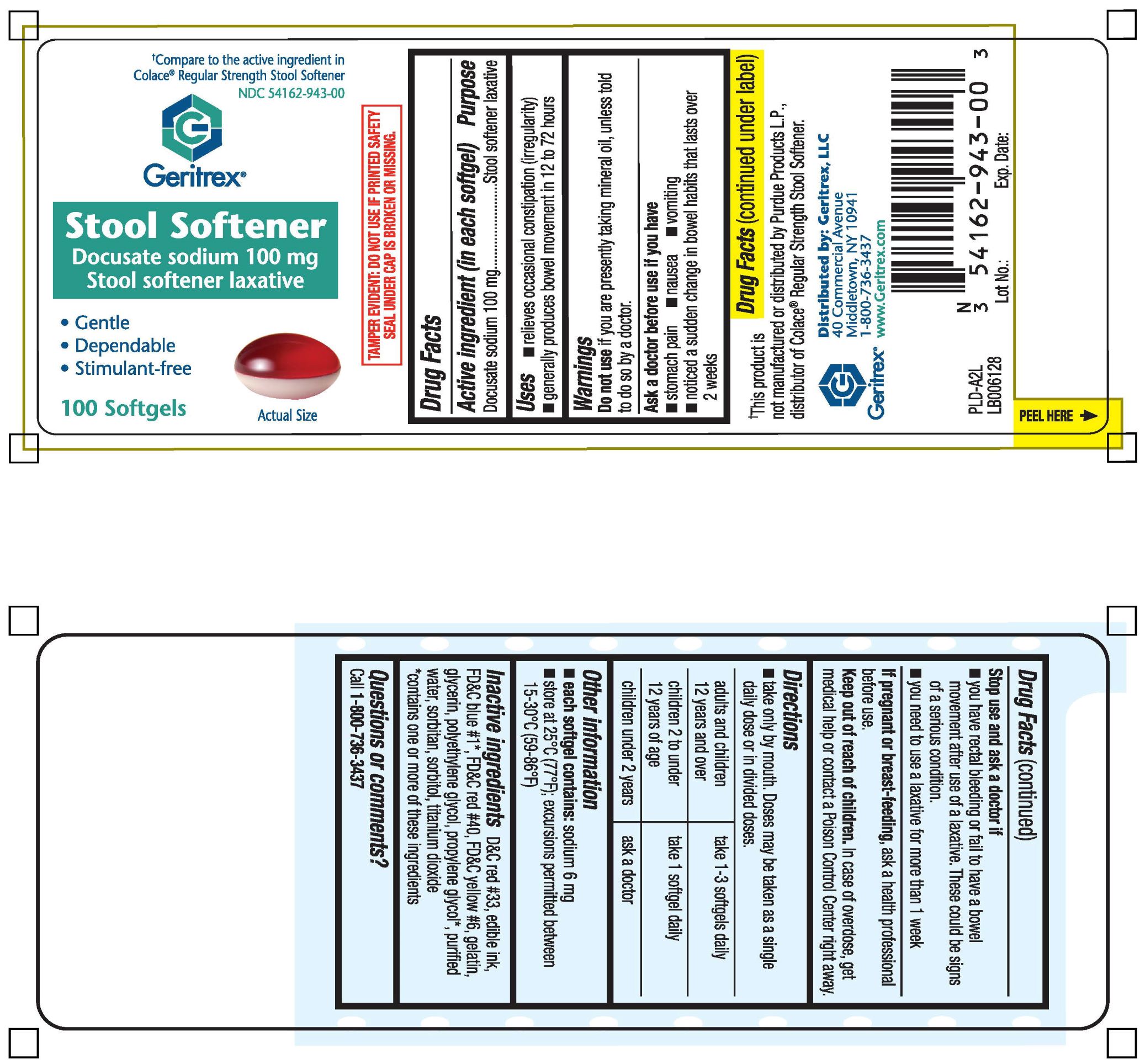 DRUG LABEL: Stool Softener
NDC: 54162-943 | Form: CAPSULE, LIQUID FILLED
Manufacturer: GERITREX LLC
Category: otc | Type: HUMAN OTC DRUG LABEL
Date: 20180907

ACTIVE INGREDIENTS: DOCUSATE SODIUM 100 mg/1 1
INACTIVE INGREDIENTS: D&C RED NO. 33; FD&C BLUE NO. 1; FD&C RED NO. 40; FD&C YELLOW NO. 6; GELATIN; WATER; SORBITAN; SORBITOL; TITANIUM DIOXIDE

DOCUSATE SODIUM

Active ingredient (in each softgel)

Docusate Sodium 100 mg

Purpose

Stool softener laxative

Uses

- relieves occasional constipation (irregularity)
- generally produces bowel movement in 12 to 72 hours

Warnings

Do not use if you are presently taking mineral oil, unless told to do so by a doctor.

Ask a doctor before use if you have

- stomach pain
- nausea
- vomitting
- notice a sudden change in bowel habits that lasts over 2 weeks

Stop use and ask a doctor if

- you have rectal bleeding or fail to have bowel movement after use of laxative. These could be signs of serious condition.
- you need to use a laxative for more than 1 week

If pregnant or breast-feeding,

ask a health professional before use.

Keep out of reach of children

In case of accidental overdose, get medical help or contact a Poison Control Center right away

Directions

take only by mouth. Doses may be taken as a single daily does or in divided doses.

Adults and children 12 years and over | take 1-3 softgels daily
Children 2 to under 12 years of age | take 1 softgel daily
Children under 2 years | ask a doctor

Other Information

- each softgel contains: sodium 6 mg
- store at 25°C (77°F); excursions premitted between 15-30°C (59-86°F)

Inactive ingredients

D&C red #33, editable ink, FD&C blue #1*, FD&C red #40, FD&C yellow #6, gelatin, glycerin, polyethylene glycol, propylene glycol*, purified water, sorbitan, sorbitol, titanium dioxide
*contains one or more of these ingredients.

Questions or comments?

Call 1-800-736-3437